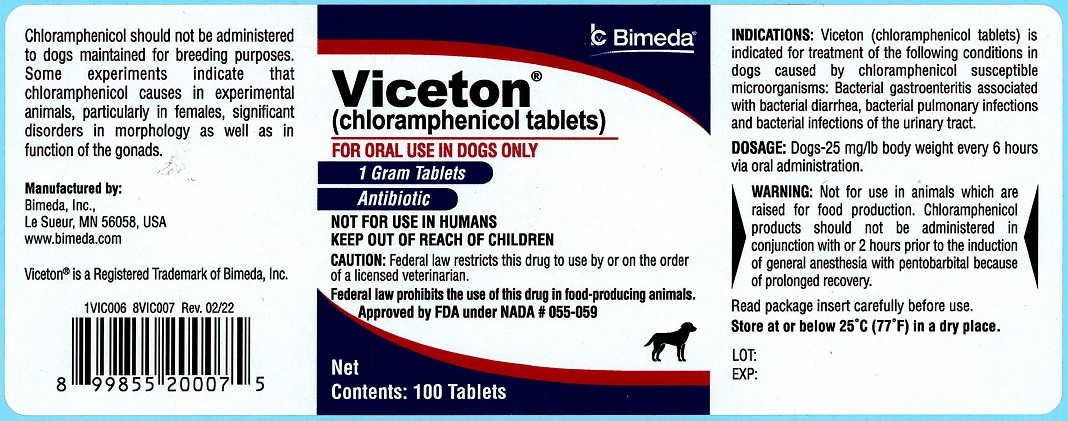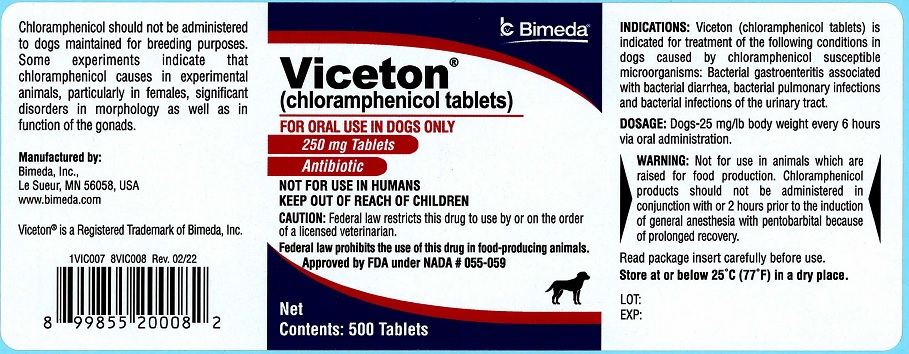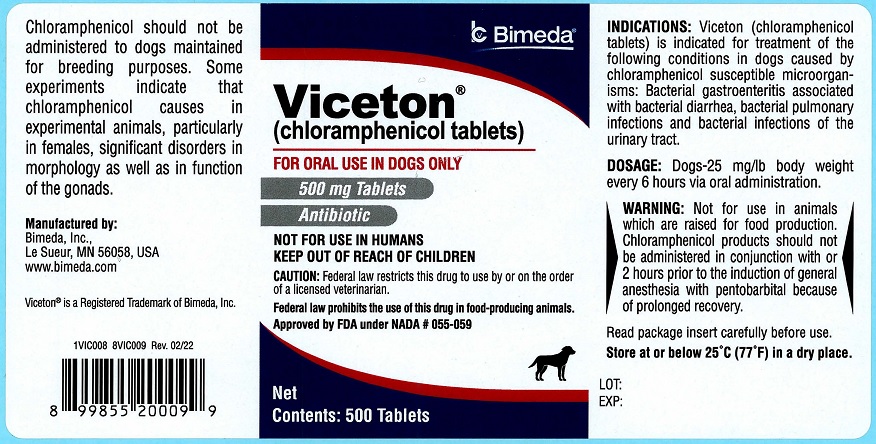 DRUG LABEL: Viceton
NDC: 61133-2212 | Form: TABLET, COATED
Manufacturer: Bimeda, Inc.
Category: animal | Type: PRESCRIPTION ANIMAL DRUG LABEL
Date: 20241227

ACTIVE INGREDIENTS: CHLORAMPHENICOL 250 mg/1 1

DESCRIPTION

Viceton®

(chloramphenicol tablets)

CAUTION: Federal law restricts this drug to use by or on the order of a licensed veterinarian.

DESCRIPTION:

Chloramphenicol is a broad-spectrum antibiotic shown to have specific therapeutic activity against a wide variety of organisms. Its activity was first demonstrated in culture filtrates from a species of soil organism collected in Venezuela, later designated as Streptomyces venezuelae. The antibiotic was subsequently isolated from culture filtrates (1), identified chemically (2), and later synthesized (3).

Aqueous solutions of chloramphenicol are neutral in pH. Chloramphenicol is stable for several years at room temperature and forms colorless to yellowish-white crystals in the shape of elongated plates or fine needles. It is only slightly soluble in water, but soluble in alcohol and propylene glycol.

Chloramphenicol is exceptionally stable in the presence of high pH, although it is destroyed at pH's in excess of 10. Dissolved in distilled water, it can withstand boiling for five hours (1).

ACTIONS:

At low concentrations, chloramphenicol exerts a bacteriostatic effect on a wide range of pathogenic organisms, including many Gram-positive and Gram-negative bacteria, spirochetes, several rickettsiae and certain large viruses and Mycoplasma (PPLO) (4,5,6,7,8,9,10,11,12,13, and 13a). At high concentrations, it inhibits growth of animal and plant cells.

Chloramphenicol exerts its bacteriostatic action by inhibiting protein synthesis in susceptible organisms. Complete suppression of the assimilation of ammonia and of the incorporation of amino acids, particularly glutamic acid, together with an increased formation of ribonucleic acid (RNA), lead to an inhibition of bacterial growth (4, 14, 15, 16, and 17).

Chloramphenicol antagonizes the action of such antibiotics as penicillin and streptomycin, which act only on growing cells, but is synergistic to tetracycline, which also acts by inhibiting protein synthesis. (18) It is possible the chloramphenicol would produce similar synergism with other antibiotics which act by inhibiting protein synthesis.

In this respect, the experimentally demonstrated synergistic action between chloramphenicol and gamma-globulin should be mentioned. Clinical observations in man and corresponding investigations in laboratory animals experimentally infected with various pathogenic bacteria have shown that a combination of chloramphenicol with gamma-globulin or specific antisera has a greater therapeutic effect than would be expected from a mere addition of the individual effects (19,20, 21, and 22).

Many experiments have revealed that the development of resistance to chloramphenicol is rare compared with that occurring with other important antibiotics. (23, 24, 25, 26, 27, 28, 29, 30, 31, 32, 33, and 34) Bacterial resistance may develop in some strains against chloramphenicol but has been encountered only infrequently in clinical usage.

Chloramphenicol achieves maximum serum levels very rapidly following oral, intravenous and intraperitoneal administration. Intramuscular injection with chloramphenicol, except certain soluble forms, results in a somewhat delayed absorption and lower serum levels than when given by the oral, intravenous, or intraperitoneal route.

Chloramphenicol diffuses readily into all body tissues, but at different concentrations. Highest concentrations are found in the liver and kidney of dogs indicating that these organs are the main route of inactivation and excretion of the metabolites. The lungs, spleen, heart and skeletal muscles contain concentrations similar to that of the blood (27, 35, 36, 37, 38, and 39).

Chloramphenicol reaches significant concentration in the aqueous and vitreous humors of the eye from the blood (4).

A significant difference from other antibiotics is its marked ability to diffuse into the cerebrospinal fluid. Within three to four hours after administration, the concentration in the cerebrospinal fluid has reached, on the average, 50% of the concentration in the serum. If the meninges are inflamed, the percentage may be even higher (4, 27, 29, 40, 41, 42, and 43).

Chloramphenicol diffuses readily into milk, pleural and ascitic fluids and crosses the placenta attaining concentrations of about 75% of that of the maternal blood (36 and 44).

Chloramphenicol is rather rapidly metabolized, mainly in the liver, by conjugation with glucuronic acid.

Approximately 55% of a single daily dose can be recovered from the urine of a treated dog. A small fraction of this is in the form of unchanged chloramphenicol (36).

A single intravenous dose of 150 mg/kg (approximately 68 mg/lb) in propylene glycol is the maximum dose tolerated by the dog. (45) No toxic effect was observed when dogs were administered orally, 200 mg/kg (approximately 91 mg/lb) daily for over four months. (40) In the mouse, the LD-50 is 150-250 mg/kg (68 to 114 mg/lb) body weight by intravenous injection and 1,500 mg/kg (approximately 681 mg/lb) by the oral administration (1 and 46).

INDICATIONS:

Chloramphenicol Tablets are recommended for oral treatment of the following conditions in dogs:

- Bacterial pulmonary infections caused by susceptible microorganisms such as: Staphylococcus aureus, Streptococcus pyogenes and Brucella bronchiseptica.
- Infections of the urinary tract caused by susceptible microorganisms such as: Escherichia coli, Proteus vulgaris, Corynebacterium renale, Streptococcus spp., and hemolytic Staphylococcus.
- Enteritis caused by susceptible microorganisms such as: E. coli, Proteus spp., Salmonella spp., and Pseudomonas spp.
- Infections associated with canine distemper caused by susceptible microorganisms such as: B. bronchiseptica, E. coli, P. aeruginosa, Proteus spp., Shigella spp. and Neisseria catarrhalis.

Additional adjunctive therapy should be used when indicated. Most susceptible infectious disease organisms will respond to chloramphenicol therapy in three to five days when the recommended dosage regimen is followed. If no response to chloramphenicol therapy is obtained in three to five days, discontinue its use and review the diagnosis. Also, a change of therapy should be considered.

Laboratory tests should be conducted including in vitro culturing and susceptibility tests on samples collected prior to treatment.

CONTRAINDICATIONS:

Because of potential antagonism, chloramphenicol should not be administered simultaneously with penicillin or streptomycin.

WARNING:

NOT FOR USE IN ANIMALS WHICH ARE RAISED FOR FOOD PRODUCTION. CHLORAMPHENICOL PRODUCTS SHOULD NOT BE ADMINISTERED IN CONJUNCTION WITH OR 2 HOURS PRIOR TO THE INDUCTION OF GENERAL ANESTHESIA WITH PENTOBARBITAL BECAUSE OF PROLONGED RECOVERY.

CHLORAMPHENICOL SHOULD NOT BE ADMINISTERED TO DOGS MAINTAINED FOR BREEDING PURPOSES. SOME EXPERIMENTS INDICATE THAT CHLORAMPHENICOL CAUSES IN EXPERIMENTAL ANIMALS, PARTICULARLY IN FEMALES, SIGNIFICANT DISORDERS IN MORPHOLOGY AS WELL AS IN FUNCTION OF THE GONADS.

HAZARDS AND PRECAUTIONS:

1. This antibiotic contains a chemical structure (nitrobenzene group) that is characteristic of a group of drugs long known to depress hematopoietic activity of the bone marrow (54).
2. In vitro-tissue culture studies using canine bone marrow cells have demonstrated that extremely high concentrations of chloramphenicol inhibit both uptake of iron by the nucleated red cells and incorporation of iron into heme (55).
3. Chloramphenicol products should not be administered in conjunction with or two hours prior to the induction of general anesthesia with pentobarbitol because of prolonged recovery time.
4. Chloramphenicol products should not be administered to dogs maintained for breeding purposes. Some experiments indicate that chloramphenicol causes, in experimental animals, particularly females, significant disorders in morphology as well as in function of the gonads.

ADVERSE REACTIONS:

Certain individual dogs may exhibit transient vomiting or diarrhea after an oral dose of 25 mg/lb body weight (49).

The Safety Data Sheet (SDS) contains more detailed occupational safety information. To report suspected adverse drug events, for technical assistance or to obtain a copy of the SDS, contact Bimeda, Inc. at 1-888-524-6332. For additional information about adverse drug experience reporting for animal drugs, contact FDA at 1-88-FDA-VETS or online at www.fda.gov/reportanimalae.

DOSAGE AND ADMINISTRATION:

Dogs-25 mg/lb body weight every 6 hours for oral administration.

Keep out of reach of children.

STORAGE AND HANDLING

Store at or below 25°C (77°F) in a dry place.

HOW SUPPLIED:

250 mg...............................Bottles of 500's, 1000's

500 mg...............................Bottles of 500's

1 gram................................Bottles of 100's

Approved by FDA under NADA # 055-059

REFERENCES:

1. Ehrlich, J., Q.R. Bartz, R.M. Smith, D.A. Joslyn and P.R. Burkholder (1947): Science 106, 127.
2. Rebstock, M.C., H.M. Crooks, Jr., J. Controulis and Q.R. Bartz (1949): J. Amer. Chem. Soc. 71, 2458-2462.
3. Controulis, J., M.C. Rebstock and H.M. Crooks, Jr. (1949): J. Amer. Chem. Soc. 71, 2463-2468.
4. Barber, M. and L.P. Garrod (1963): Antibiotic and Chemo-therapy. E. and S. Livingston, Edinburgh, London: 116 to 128.
5. Christi, A.B. (1963): Practitioner 191, 588-593.
6. Lange, A. and E. Vogel (1958): Z. Hyg. infektionshrankh. 144, 555-563. Ref.: Landw. Zbl. Abt. IV, 5, 1960, 2188.
7. Schirmer, R.C., F.E. Eades and J.P. Newman (1952): Vet. Med. 46, 485-490 Ref.: Vet. Rec. 64, 1952, 597.
8. Smadel, J.E. and E.B. Jackson (1947): Science 106, 418-419.
9. Zettl, K. (1960): Vet.-Med. Nachr, 25-35.
10. Godzeski, C.W. and D.E. Pavey (1965): Nature 205, No. 4975, 1017 to 1018.
11. Hille, G. and E. Ludwig (1964): Mh. Vet.-Med. 20, 704-708.
12. Hubrig, Th. and D. Schimmel (1965): Mh. Vet.-Med. 20, 171-174.
13. Schimmel, D. and Th. Hubrig (1965): mh. Vet.-Med. 20, 334-338.

13a. Hagen, Wm. A. and Bruner, D.W. (Third Edition, 1957): The Infectious Diseases of Domestic Animals, Cornell University Press. 1479.

1. Brock, Th. D. (1963): J. Bact. 85, 527-531.
2. Brock, T.D. Chloramphenicol, Bacterial. Rev. 25: 32-48, 1961.
3. Saurat, P. and R. Lautie (1959): Rev. Med. Veterin. 22, 689-701.
4. Schaub, F. (1962): Schweiz, Arch. Tierheilk, 104, 373-384.
5. Reedy, R.J., W.W. Wright, E.J. Oswald and M. Ostrolenk (1958): Antibiot. Ann. 1957/58, 745-750.
6. Fisher, M.W. (1957) Antib. Chemoth. 7, 315-321.
7. Manning, M.C., L.A. Gagliardi and M.W. Fisher (1958): Antibiot. Ann. 1957/58, 566-571.
8. Reedy, R.J., E.J. Oswald and W.W. Wright (1958): Antibiot. Ann. 1957/58, 581-584.
9. Waisbren, B.A. (1957) Antib. Chemoth. 7, 315-321.
10. Beseth, L. (1963):Nord. Vet.-Med. 15, 745-754.
11. Gedek, W., R. Dunkel and L. Kotter (1964): Tierarztl, Umsch. 19, 337-340.
12. Kettner, H. and A. Braunsteiner (1960): Tierarztl, Umsch. 15, 249-255.
13. Kortum, H. (1963): Vet. Med. Diss. Munchen.
14. Kraft, H. (1960): Tierarztl, Umsch. 15, 58-60.
15. Kraft, H. (1962): Tierarztl, Umsch. 17, 278-280.
16. Lettow, E. (1954): Tierarztl, Umsch. 9, 227-230.
17. Manten, A., E.H. Kampelmacher and P.A.M. Guinee (1963): T. Dierganeesk. 88, 411-417.
18. Palyusik, M. (1963)" Mag. allator. Lapja 18, 356-357. Ref.: Vet Bull. 34, 1964, 317.
19. Ramsay, C.H. and P.R. Edwards (1961): Appl. Microbiolog. 9, 389-391.
20. Smith, H.W. (1954): Vet. Rec. 66, 42-43.
21. Smith, W. H. and W.E. Crabb (1956): Vet. Rec. 68, 274-277.
22. English, P.B. and A.A. Seawright (1961): Aust. Vet. J. 37, 9-13.
23. Glazko, A.J., L.M. Wolf, W.A. Dill and A.C. Bratton, Jr. (1949): J. Pharmacol. exp. Ther. 96, 445-449.
24. Glazko, A.J., H.E. Carnes, A. Kazenko, L.M. Wolf and T.F. Teutner (1958): Antibiot. Ann. 1957/58, 792-802.
25. Eads, F.E., A.J. Glazko, L.M. Wolf, J.Erlich and M. Galbraith (1952): Amer. J. Vet. Res. 13, 204-206.
26. Leopold, I.H., Nichols, A.C. and Voegl, A.W., Penetration of Chloramphenicol U.S>P. (Chloromycetin) into the Eye. Arch. Ophth., 44:22, 1950.
27. Gruhzit, O.M., R.R. Risken, T.F. Reutner and E. Martino (1949): J. Clin. Invest. 28, 943-951.
28. McCrumb, Jr., R.R., M.J. Snyder and W.J. Hicken (1958): Antibiot. Ann. 1957/58, 837-841.
29. Ross S.H. Bischoff, W. Preissner and W. Orr (1949): J. Clin. Invest. 28, 1050.
30. Roy, T.E., E. Krieger, G.Craig, D. Cohen, G.A. McNaughton and N. Silverthorne (1952): Antib. Chemoth. 2, 505-516.
31. Walter, M. and L. Heilmeyer (1954): Antibiotika-Fibel. Georg Thieme Verlag, Stuttgart, 1954.
32. Ehrlich, J. chloramphenicol. Encyclopedia of Chemical Technology. 4: 928-936, 1964.
33. Cheymol, J. (1955): Arzeimeittel Forsch. 5, 1-9.
34. Smith, R.M., D.A. Joslyn, O.M. Gruhzit, I.W. McLean, M.A. Penner and J. Ehrlich (1948): J Bact. 55, 425-448.
35. Van Looveren, L.J. (1958): Schweiz. Arch. Tierheilk, 100, 459-467.
36. Sogtrop, H.H. (1956): Tierarztl, Umsch. 11, 257-261.
37. Hrenoff, A.K. (1962): Med. exp. 6, 118-122.
38. Nelson, A.A. and J.L. Radomski (1954): Antib. Chemoth 4, 1174-1180.
39. Reutner, T.F., R.E. Maxwell, K.E. Weston and J.K. Weston (1955): Antib. Chemoth. 5, 679-711.
40. Weston, J.D., T.F. Reutner ,R.Q. Thompson and R.E. Maxwell (1954): Fed. Proc. 13, 416.
41. Jones, L.M., Veterinary Pharmacology and Therapeutics, 3rd Edition, Iowa State University Press, Ames, Iowa, 539-542, 1965.
42. Ward, H.P., The Effect of Chloramphenicol on RNA and Heme Synthesis in Bone Marrow Cultures. Journ. Lab and Clinical Med., 68: 403, 1966.
43. The Merck Veterinary Manual, 2nd Edition, Merck and Co., Inc., Rahway, N.J., 522-524, 1961.